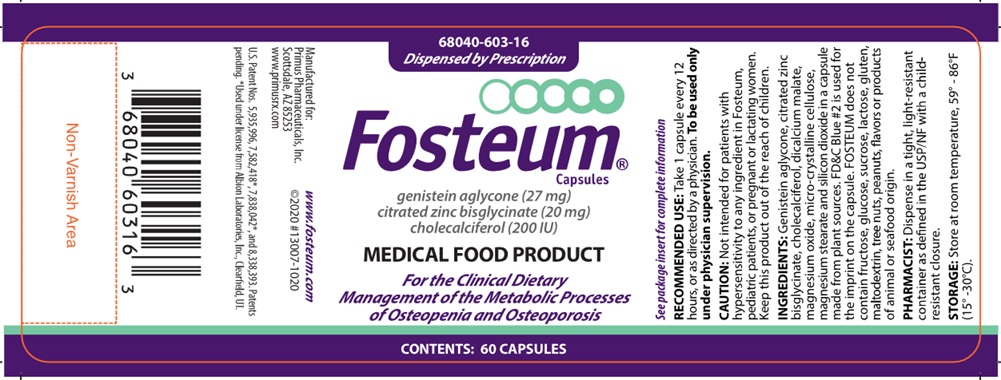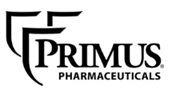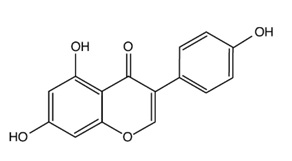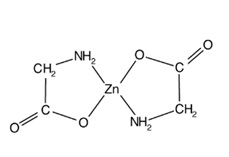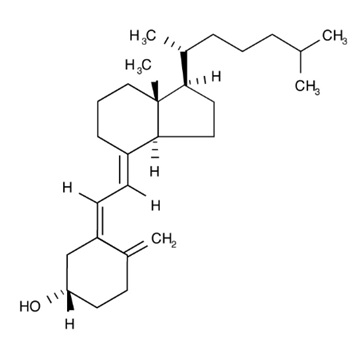 DRUG LABEL: Fosteum
NDC: 68040-603 | Form: CAPSULE
Manufacturer: Primus Pharmaceuticals, Inc.
Category: other | Type: MEDICAL FOOD
Date: 20250219

ACTIVE INGREDIENTS: GENISTEIN 27 mg/1 1; ZINC GLYCINATE CITRATE 20 mg/1 1; CHOLECALCIFEROL 200 [iU]/1 1
INACTIVE INGREDIENTS: MAGNESIUM OXIDE; CELLULOSE, MICROCRYSTALLINE; MAGNESIUM STEARATE; SILICON DIOXIDE; FD&C BLUE NO. 2; DICALCIUM MALATE DIHYDROXIDE

FOSTEUM® Capsules
genistein aglycone (27 MG)
citrated zinc bisglycinate (20 MG)
cholecalciferol (200 IU)

FOSTEUM® is a specially formulated prescription medical food product for the clinical dietary management of the metabolic processes of osteopenia and osteoporosis. FOSTEUM must be administered under physician supervision.

DESCRIPTION

FOSTEUM consists of a specially formulated proprietary blend of high purity genistein aglycone from a natural source, citrated zinc bisglycinate and cholecalciferol (vitamin D3). Genistein aglycone reduces osteoclast activity and stimulates osteoblast activity. Citrated zinc bisglycinate works synergistically with genistein aglycone, while both citrated zinc bisglycinate and vitamin D3 also work independently to promote mineralization activity in bone. Vitamin D3 also facilitates calcium absorption from the intestine.

Genistein aglycone

Each FOSTEUM capsule contains 27 mg of genistein aglycone (genistein), derived from a natural source, for a total daily intake of 54 mg. In clinical trials, this level of intake has been shown to increase bone mineral density (BMD). Genistein is chemically described as 4',5,7-trihydroxyisoflavone or 5,7-dihydroxy-3-(4-hydroxyphenyl)-4H-1-benzopyran-4-one. It is the aglycone form of the glucoside isoflavone molecule genistin. The empirical formula of genistein is C15H10O5; its molecular weight is 270.2. The structural formula is:

Citrated zinc bisglycinate

Each FOSTEUM capsule contains 20 mg citrated zinc bisglycinate, a glycine amino acid chelate of zinc formed in the presence of citric acid that provides approximately 4 mg of elemental zinc per capsule. Zinc is an essential mineral co-factor required by enzymes involved in bone metabolism and has important physiological functions in other tissues throughout the body. Elemental zinc has also been shown to have synergistic effects with genistein on bone formation. This zinc bisglycinate, formed in the presence of citric acid, has been shown to have improved absorption over inorganic zinc salts, such as zinc sulfate. Zinc bisglycinate, a chelate of zinc, is complex with an empirical formula of C4H8O4Zn; its molecular weight is 215.5. Its structural formula is:

When generated in the presence of citric acid, citrate and additional glycinate ions (not shown) also participate in this structure, forming citrated zinc bisglycinate, contributing to the complexity of the molecule.

Cholecalciferol

Each FOSTEUM capsule contains cholecalciferol equivalent to 200 IU vitamin D3. Vitamin D3 is the natural form of vitamin D3 produced when skin is exposed to the sun. Vitamin D is necessary for proper absorption of calcium from the intestine and the use of absorbed calcium in the mineralization of bone. Cholecalciferol is the natural precursor of calcitriol (1,25-dihydroxy-cholecalciferol), the physiologically active form of vitamin D3. It is described as (3ßμ,5Z,7E)-9,10-secocholesta-5,7,10(19)-triene-3-ol. The empirical formula is C27H44O; its molecular weight is 384.6. The structural formula is:

Other Ingredients

FOSTEUM contains the following other ingredients as excipients: dicalcium malate, magnesium oxide, micro-crystalline cellulose, magnesium stearate and silicon dioxide in a capsule made from plant sources. FD&C Blue #2 is used for the imprint on the capsule. FOSTEUM does not contain fructose, glucose, sucrose, lactose, gluten, maltodextrin, tree nuts, peanuts, soy, flavors or products of animal or seafood origin. FOSTEUM is suitable for vegans.

Medical Food

Medical Food products are used under a physician's supervision for the dietary management of diseases in patients with particular medical or metabolic needs due to their disease or condition. The U.S. Congress defined "medical food" in the Orphan Drug Act and Amendments of 1988 as "a food which is formulated to be consumed or administered enterally under the supervision of a physician, and which is intended for the specific dietary management of a disease or condition for which distinctive nutritional requirements, based on recognized scientific principles, are established by medical evaluation." FOSTEUM has been developed, manufactured and labeled in accordance with both the statutory and the FDA regulatory definition of a medical food. FOSTEUM is to be used only under a physician's supervision.

Generally Recognized As Safe

The ingredients in FOSTEUM are Generally Recognized As Safe (GRAS). This is the statutory safety standard that the U.S. Food and Drug Administration (FDA) requires of all ingredients added to food products. The standard for an ingredient to achieve GRAS status requires technical demonstration of non-toxicity and safety, general recognition of safety through widespread usage and agreement of that safety by experts in the field.

LOW BONE MASS AND OSTEOPOROSIS

Low bone mass (osteopenia) and osteoporosis are gradations of bone loss. Low bone mass may progress to osteoporosis. Low bone mass and osteoporosis occur when the metabolic processes of normal bone turnover is unbalanced in favor of resorption activity. The World Health Organization (WHO) defines low bone mass as a T-score (by dual energy absorption technology, DXA) between -1.0 and -2.5. Osteoporosis is defined at a T-score lower than -2.5.

CLINICAL PHARMACOLOGY

Mechanism of Action

FOSTEUM acts by restoring and maintaining the balance of bone turnover toward normal levels in osteopenia and osteoporosis. Preclinical and clinical data suggest that the genistein in FOSTEUM both reduces osteoclast-mediated bone resorption and stimulates the bone forming activity of osteoblasts. The zinc in FOSTEUM acts synergistically with the genistein, and the cholecalciferol improves the absorption of calcium and its deposition into the mineral matrix of bone.

Osteopenia and osteoporosis generally occur because of hormonal changes associated with the aging process or the use of certain classes of drugs. Bone loss associated with these conditions is primarily due to the metabolic imbalance that occurs when osteoclast activity is greater than osteoblast activity. The imbalance of bone resorption in excess of bone formation is progressive and often leads to fractures. These minimal trauma fractures may lead to significant morbidity and mortality. Successful dietary management of the metabolic processes underlying osteopenia and osteoporosis helps to restore the balance between bone resorption and bone formation and consequently increases bone density over time.

Genistein aglycone

The genistein in FOSTEUM reduces the activity of osteoclasts and promotes the formation of osteoblasts from progenitor stem cells to increase their number and activity in bone. The net effect is an enhancement of bone formation which restores bone remodeling toward normal levels and results in an increase in bone mineral density (BMD) over time. Through these clinical dietary modifications, FOSTEUM manages the metabolic processes of osteopenia and osteoporosis.

More specifically, preclinical studies suggest the following mechanisms of action: Genistein acts to reverse the effects of estrogen loss by decreasing cytokine production and increasing transforming growth factor ß (TGFß) levels. The net effect is a decrease in receptor activator of nuclear factor kappa B ligand (RANK-L) production, an increase in osteoprotegerin (OPG) levels, and interruption of the interaction between RANK and RANK-L which as a consequence, decreases overall osteoclast activity. Genistein also increases insulin-like growth factor-1 (IGF-1) leading to an increased number of proto-osteoblasts developed from mesenchymal stem cells. Genistein restores endothelial cell signals resulting in increased recruitment of these precursor cells to form osteoblasts. Genistein also reverses early apoptosis of osteoblasts. These actions likely produce a net increase in osteoblast activity and concomitant decrease in osteoclast activity.

In clinical trials, the genistein in FOSTEUM decreased urinary levels of the bone resorption markers urinary and serum collagen type 1 cross-linked C-telopeptide (CTX), deoxypyridinoline (DPYR) and pyridinoline (PYR), and increased serum levels of the bone formation markers bone-specific alkaline phosphatase (BAP), osteocalcin (OC), and IGF-1 and increased BMD over time.

Zinc (Elemental)

Studies have shown that zinc has a positive effect on bone formation. The zinc in FOSTEUM is the citrated bisglycinate form, which has been shown to have improved absorption from the intestine compared to inorganic zinc salts.

Cell cultures of rat femoral-metaphyseal tissue treated with zinc and genistein produced a greater increase in BAP, DNA and bone calcium content compared with either agent alone. Other studies have demonstrated that genistein and zinc produce synergistic effects on osteoclast apoptosis and bone mineralization. Animal studies support these findings by showing that the combination of zinc and genistein increases mineralization in bone over genistein alone. In both men and women, zinc was shown to potentiate the effect of high genistein-containing fermented food on bone markers by further increasing the levels of BAP and OC. Based on these data, genistein and zinc increase osteoblast activity while decreasing osteoclast activity to a greater extent than either genistein or zinc alone.

Cholecalciferol

The physiologically active form of vitamin D, calcitriol, regulates calcium and phosphate absorption and modulates serum calcium, renal calcium and phosphate excretion, bone formation and bone resorption. Vitamin D deficiency is associated with a negative calcium balance, increased parathyroid hormone levels, bone loss and increased risk of skeletal fracture. Severe deficiency results in hyperparathyroidism, hypophosphatemia, bone loss, proximal muscle weakness and osteomalacia.

METABOLISM

Genistein

The genistein in FOSTEUM is freely absorbed in the gut where it is at least partly converted to one metabolite, 7-O-beta-glucuronide, before it crosses the mucosa from the intestinal lumen. In hepatic first pass metabolism, genistein is converted via a two-stage process involving initial CYP450-mediated hydroxylation, followed by glucuronidation and sulfonation to the principal conjugated circulating metabolites. Genistein metabolites are converted back into the aglycone form in a variety of tissues. The aglycone is believed to be the principal active form, but conjugates have shown some activity in estrogen-receptor binding assays. Genistein and its conjugates are excreted via urine and bile.

Citrated zinc bisglycinate consists of zinc chelated by glycine in the presence of citric acid. Once absorbed, the zinc is released from the chelate. Subsequently, glycine is utilized in normal protein metabolism and zinc is bound to albumin as well as blood cells and distributed throughout the body. The citrate is absorbed and utilized in the tricarboxylic acid cycle (Krebs cycle). The majority of zinc in the human body is found in muscle and bone. Excretion occurs predominantly via the feces.

Cholecalciferol

Ultraviolet light acts on 7-dehydrocholesterol (provitamin D3) in skin, where it is converted to 9,10-secosterol (previtamin D3). Previtamin D3 is converted into 25-hydroxycholecalciferol in the liver by the P450 enzyme CYP27. This molecule is further converted in the kidney by the P450 enzyme CYP27B1 to the active hormone 1,25-dihydroxycholecalciferol (calcitriol).

CLINICAL EXPERIENCE

Hepatic and Renal Effects

In clinical studies, the effects of genistein in FOSTEUM on blood chemical, hepatic and renal functional measures were compared in post-menopausal subjects receiving genistein plus calcium carbonate (calcium) and vitamin D3 with post-menopausal, age-matched subjects receiving only calcium and vitamin D3. No change in laboratory values were noted over a three year period in either group and all measures remained within normal limits.

Since the precursor form of vitamin D3 is transformed to the active form in the liver and then kidney, it is expected that patients with severe liver or kidney impairment may not transform the vitamin adequately.

Effects on Reproductive Tissues

Effects of the genistein in FOSTEUM on breast density, vaginal cytology and endometrial thickness were tested in double-blind, placebo-controlled clinical trials. One trial with 30 post-menopausal subjects in each arm found that genistein did not affect endometrial thickness over a one year period compared to placebo. In other controlled trials, daily administration of 54 mg of genistein over one, two and three year periods produced no increases in endometrial thickness or breast density in post-menopausal women. Furthermore, a subset of 119 post-menopausal women showed no change in vaginal cytology following two years of daily genistein therapy. These data suggest that the genistein in FOSTEUM does not produce adverse estrogenic effects in reproductive tissues.

Cardiovascular Safety

In a study of 60 post-menopausal subjects comparing the cardiovascular markers of those receiving thegenistein in FOSTEUM to a matched group receiving placebo, homocysteine and C-reactive protein (CRP)were assessed at baseline and again at 6 months. No statistically significant differences were seenbetween groups. Soluble intercellular adhesion molecule-1 (ICAM), vascular cell adhesion molecule-1(VCAM), fibrinogen and F2-isoprostane levels were assessed at baseline and again at 12 and 24 months in389 post-menopausal subjects randomized to receive either genistein, calcium and vitamin D3 or calciumand vitamin D3 only (placebo). At both 12 and 24 months, the levels of all four cardiovascular markers werereduced in the genistein group compared to both baseline and placebo at all time points. No significantchanges in lipid profile were observed in either the genistein or placebo group over the course of the study.These data indicate that genistein does not adversely affect markers of cardiovascular risk. An additionalstudy of 53 post-menopausal women measured changes in flow-mediated vasodilation and plasma nitricoxide status. The genistein in FOSTEUM significantly increased plasma nitrite/nitrate levels and reducedlevels of endothelin-1 compared to placebo. After 12 months of use, forearm blood flow increasedsignificantly during reactive hyperemia in the genistein group compared to placebo. Flow-mediated dilationin the proximal and distal brachial arteries both increased significantly after genistein administration. Thepurified genistein in FOSTEUM improved endothelial function in a cohort of post-menopausal women.

Menopausal Symptoms

In three published studies with a combined enrollment of more than 300 post-menopausal women, the genistein in FOSTEUM progressively reduced the number of symptomatic vasomotor episodes by an average of more than 50% at the 24 month follow-up. In these studies, vasomotor symptoms were unchanged in the placebo groups.

Blood Glucose and Insulin Resistance

The genistein in FOSTEUM was also found to significantly reduce fasting glucose and insulin levels, as well as insulin resistance, in 198 post-menopausal women over a 2 year period and in a subset of 71 patients over a 3 year period when compared to placebo.

DRUG INTERACTIONS

Genistein

The genistein in FOSTEUM was tested in in vitro pooled human liver microsome assays for CYP1A2, 2A6, 2C8, 2C9, 2D6, and 3A4. Inhibition of the 1A2, 2A6, 2D6 and 3A4 isozymes was low, however, inhibition of CYP450 2C8 and 2C9 was observed with IC50s of 2.5 and 2.8 μM, respectively. Results from a steady-state pharmacokinetic study in post-menopausal women showed that the level of circulating genistein was in the low nanomolar range and undetectable at most time points in many subjects. These data suggest that circulating genistein does not reach concentration required to produce any clinically significant interactions with co-administered drugs. The effects of the principal circulating metabolites of genistein on CYP450-mediated metabolism are currently unknown.

Cholecalciferol

Cimetidine, thiazides and anticonvulsants may increase catabolism of vitamin D3. Cholestyramine and other bile acid sequestrants, as well as mineral oil, orlistat and olestra may impede absorption of vitamin D3 from the intestine.

TOXICITY

Genistein

Genistein showed no toxicity in rats following acute dosing up to 2000 mg/kg. Long-term toxicity studies up to 52 weeks duration using oral administration of 0-500 mg/kg/day in rats and dogs showed minimal adverse effects. Changes were primarily observed at the 500 mg/kg/day dose. From these studies, the no observed adverse effect level for genistein in rats was determined to be 50 mg/kg/day and in dogs >500 mg/kg/day. These intake levels are at least 50-fold greater than the recommended dose of the genistein in FOSTEUM on a mg/kg basis.

Zinc (Elemental)

The National Academy of Sciences (NAS) upper acceptable limit for self-administration is 40 mg/day of elemental zinc, the equivalent of ten FOSTEUM capsules per day. Zinc is considered acutely toxic at 200 mg elemental zinc per day, the equivalent of 50 FOSTEUM capsules per day.

Cholecalciferol

Cholecalciferol may produce toxicity with long term, high-dose consumption. While medical doses of vitamin D3 up to 10,000 IU per day are sometimes administered under physician supervision, the upper acceptable limit for self-administration is 2,000 IU per day per the Daily Reference Intakes of the Institute of Medicine published by the NAS in 2004. Signs and symptoms of vitamin D toxicity include hypercalcemia, hypercalciuria, anorexia, nausea, vomiting, polyuria, polydipsia, weakness and lethargy. Serum and urine calcium levels should be monitored in patients with suspected vitamin D toxicity. Standard therapy includes restriction of dietary calcium, hydration and systemic glucocorticoids in patients with severe hypercalcemia.

SPECIAL POPULATIONS

Pregnant or Nursing Women

FOSTEUM has not been tested in pregnant or nursing women.

Males

FOSTEUM has not been studied for its effect on bone in human males. No specific studies on genistein aglycone and feminization in human males exist.

Pediatrics

FOSTEUM has not been tested in pediatric patients.

INDICATIONS AND USAGE

Indications

FOSTEUM is indicated for the clinical dietary management of the metabolic processes of osteopenia and osteoporosis.

Usage

FOSTEUM should be taken with sufficient calcium and vitamin D3 as directed by a physician. In clinical trials of the genistein in FOSTEUM, patients also received 1,000 mg of calcium carbonate and 800 IU vitamin D3 per day in two divided doses. See Dosage and Administration for additional information.

Interactions with Food

FOSTEUM can be taken with or without other foods. FOSTEUM may be taken with any beverage desired.

PRECAUTIONS AND CONTRAINDICATIONS

General

Causes of osteopenia or osteoporosis other than menopause or aging should be considered.

Hypersensitivity

FOSTEUM is contraindicated for anyone having a hypersensitivity to any ingredient in the product. See "Other ingredients" for a full list of ingredients.

Patients with Cancer

FOSTEUM has not been specifically studied in patients with a history of cancer of the breast or reproductiveorgans. Major studies on isoflavone intake have been published including one epidemiological studyinvolving 18,312 postmenopausal women who were followed for an average of 9.2 years. Based on thesefindings, FOSTEUM may be suitable for the management of osteopenia and osteoporosis in thesepopulations. The decision to use FOSTEUM in these clinical situations should be made in consultation withthe patient’s physician.

Vitamin D Deficiency

FOSTEUM is not intended to treat vitamin D deficiency, generally characterized in the literature by serum levels of 25-hydroxycholecalciferol below 9 ng/mL. FOSTEUM contains 400 IU cholecalciferol in two recommended capsules per day, but the NAS recommended daily dose in patients over the age of 70 is 600 IU/day. FOSTEUM should be taken with a calcium/vitamin D3 supplement sufficient to meet the daily requirement or as recommended by a physician. Patients with gastrointestinal malabsorption or those on certain drugs (see Drug Interactions, Cholecalciferol) may require higher doses of vitamin D3 and measurement of serum levels of 25-hydroxycholecalciferol may be indicated in this population.

Pregnancy

Animal studies suggest that genistein may produce developmental abnormalities of the male and female genital tracts if consumed during early stages of pregnancy. Effects in infants of nursing mothers are uncertain. Therefore, FOSTEUM is contraindicated in pregnant and lactating women. Women capable of becoming pregnant should use appropriate contraception when taking FOSTEUM. The genistein in FOSTEUM has not been tested in women capable of becoming pregnant.

ADVERSE EVENTS

In a three-year clinical trial, 389 subjects were randomized to either genistein plus calcium and vitamin D3 n=198, or calcium and vitamin D3 alone n=191. A total of 52 subjects in both groups discontinued due to adverse events. Study discontinuation in these subjects was due to gastrointestinal symptoms, including abdominal and epigastric pain, dyspepsia, vomiting and constipation. Discontinuation was reported in both groups. The incidence of adverse events was statistically higher in the genistein group over both years of the study. The major adverse events are shown in the table below without attribution of causality.

Adverse Events | Year 1 |  | Year 2 |  | Year 3
Adverse Events | Genistein+Ca/D3; (n=178) | Ca/D3; (n=172) | Genistein+Ca/D3; (n=150) | Ca/D3; (n=154) | Genistein+Ca/D3; (n=71) | Ca/D3; (n=67)
Abdominal Pain | 4 (2.2%) | 2 (1.1%) | 2 (1.3%) | 1 (0.6%) | 1(1.4%) | 1(1.5%)
Dyspepsia | 2 (1.1%) | 1 (0.6%) | 7 (4.7%) | 2 (1.3%) | 2(2.8%) | 1(1.5%)
Constipation | 5 (2.8%) | 3 (1.7%) | 8 (5.3%) | 3 (1.9%) | 2(2.8%) | 1(1.5%)

Some of these adverse event occurrences may be attributable to the intake of 1,000 mg per day of calcium carbonate by subjects in both groups. Taking FOSTEUM with food may reduce or eliminate some gastrointestinal symptoms.

PHARMACOKINETICS

Genistein

To determine the disposition of the genistein in FOSTEUM, a steady-state pharmacokinetic (PK) study was conducted in post-menopausal women aged 50-66. Ten subjects took FOSTEUM without food (fasted group) and 10 subjects took FOSTEUM with food (fed group) twice daily for seven (7) days. On the eighth day, blood was collected at 1, 2, 3, 4, 6, 8, 10, 12, 24, 36, 48 and 96 hours after ingesting FOSTEUM with (fed group) or without (fasted group) food. Concentrations of serum aglycone (protein bound and unbound) and total genistein (aglycone plus circulating conjugated forms) were determined at each time point for standard pharmacokinetic analyses.

Levels of free genistein aglycone were in the low nanomolar range and below the level of quantification in several subjects. Therefore, meaningful pharmacokinetic parameters could not be calculated from the data. Consistent with previous studies, the majority of circulating genistein existed in the conjugated form. Pharmacokinetic analyses for total genistein reported in the table below revealed no significant difference in any parameter between the fed and fasted groups, suggesting that FOSTEUM may be taken with or without food. The serum half-life (t1/2) among all subjects was 9.6 hours. Based on this profile, BID is recommended.

Prandial State | N | Total Genistein | Mean ±SD
Fasting | 10 | Cmax (ng/mL); Tmax (hours); T1/2 (hours); AUC | 837.5 ± 414.8; 2.0 ± 1.2; 8.1 ± 4.9; 9622.8 ± 5843.0
Fed | 9 | Cmax (ng/mL); Tmax (hours); T1/2 (hours); AUC | 671.1 ± 297.1; 3.3 ± 1.5; 11.2 ± 3.6; 11045.2 ± 6208.6

CLINICAL STUDIES

Dietary Management of Osteopenia and Osteoporosis

Effect on Bone Mineral Density

Efficacy of the genistein in FOSTEUM was demonstrated in a multi-center, double-blind, placebo-controlled clinical study of 389 randomized post-menopausal patients with osteopenia or osteoporosis (genistein n=198; placebo n=191). All subjects received calcium (1,000 mg/day) and vitamin D3 (800 IU/day) in two divided doses.

Mean Percent Change in BMD over 24 Months
SITE | 12 months vs. baseline |  | 24 months vs. baseline
SITE | Genistein +Ca/D3 (n=178) | Ca/D3 (n=172) | Genistein +Ca/D3 (n=150) | Ca/D3 (n=154)
Femoral Neck | 2.4% | -2.2% | 5.1% | -5.3%
Lumbar Spine | 2.9% | -3.6% | 5.8% | -6.3%

After two years, significant increases were seen in BMD at both lumbar spine and femoral neck relative to both baseline and placebo in patients who received genistein. In a third year extension, 138 patients continued on blinded study product. Patients taking the genistein in FOSTEUM showed a continued increase in BMD at both lumbar spine and femoral neck. In this cohort, 85% of the patients in the genistein arm showed increased BMD.

Mean Percent Change in BMD over 24 and 36 Months (Extended Study Group)
SITE | 24 months vs. baseline |  | 36 months vs. baseline
SITE | Genistein +Ca/D3 (n=71) | Ca/D3 (n=67) | Genistein +Ca/D3 (n=71) | Ca/D3 (n=67)
Femoral Neck | 5.2% | -5.4% | 7.0% | -7.5%
Lumbar Spine | 7.3% | -6.3% | 10.3% | -10.6%

Bone markers were measured and found to support the proposed mechanism of action as levels of formation markers were increased and levels of resorption markers were reduced in the genistein group compared with baseline as shown in the table below.

Mean Percent Change in Bone Markers at 12, 24 and 36 Months vs. Baseline
 | 12 months vs. baseline |  | 24 months vs. baseline |  | 36 months vs. baseline
 | Genistein + Ca/D3 (N=178) | Ca/D3 (N=172) | Genistein + Ca/D3 (N=150) | Ca/D3 (N=154) | Genistein + Ca/D3 (N=71) | Ca/D3 (N=67)
BAP | +32.7% | -0.8% | +38.5% | -1.1% | +45.3% | -1.2%
IGF-1 | +18.0% | -2.3% | +13.0% | +1.6% | +16.7% | -3.0%
PYR | -14.5% | -3.3% | -13.5% | -1.0% | -15.8% | -2.8%
DPYR | -12.4% | -1.2% | -10.2% | -0.9% | -14.1% | -3.0%
CTX | -24.9% | +2.3% | -35.5% | +2.9% | -43.7% | +6.2%

Genistein's efficacy was also shown in a one year trial of 90 osteopenic or osteoporotic, post-menopausal subjects vs. placebo and vs. HRT. Baseline values were matched for all parameters. The BMD values at 12 months are shown in the table below:

Mean Percent Change in BMD at 12 Months vs. Baseline
SITE | GENISTEIN (n=30) | HRT (n=30) | PLACEBO (n=30)
Femoral Neck | 3.6% | 2.4% | -0.7%
Ward’s Triangle | 4.0% | 3.0% | -0.4%
Lumbar Spine | 3.0% | 3.8% | -1.6%

Fracture Data

The studies that have been performed on the genistein in FOSTEUM to date have not been intended to assess new incident fractures. These studies have shown reduced markers of bone resorption, increased markers of bone formation and increased BMD in clinical trials. Anecdotally, in the 389 patient clinical trial comparing genistein to placebo over a three-year period, there were three fractures of the sacrum in the placebo (Calcium and Vitamin D3) group. No fractures were observed in the genistein group over three years. Studies in animals have demonstrated an increase in bone quality including an increase in bone breaking strength and improvement in architecture in histological examination.

Concomitant Use

No studies have been performed assessing the efficacy or safety of concomitant use of FOSTEUM with HRT, bisphosphonates, SERMs or bone anabolic agents. Since HRT, SERMs and FOSTEUM may share certain receptor targets, concomitant use of these products is not recommended.

OVER USAGE

Genistein

There are no known cases of over usage of the genistein in FOSTEUM. Animal studies have shown that consuming the equivalent of 75 FOSTEUM capsules at one time did not produce adverse events. However, as in most over usage situations, symptoms following an over usage of FOSTEUM could vary according to the patient. If an over usage were to occur, patients should be managed by systematic and supportive care as soon as possible following product consumption.

Zinc (Elemental)

Symptoms of acute zinc toxicity occur after ingestion of 2 g or more of elemental zinc, the equivalent of 500 FOSTEUM capsules at one time. Chronic zinc toxicity, resulting from induced copper deficiency, is increasingly common as the use of large doses of zinc in supplements becomes more routine. Those on long term supplementation or high doses of zinc-containing cold medication, such as zinc lozenges, should be monitored for zinc and copper status. Zinc is considered acutely toxic at 200 mg elemental zinc per day, the equivalent of 50 FOSTEUM capsules per day.

Cholecalciferol

There is limited information regarding acute vitamin D3 toxicity in humans. Single doses of ergocalciferol (vitamin D2) up to 600,000 IU have been given without noted toxicity. In patients suffering from diseases, such as leukemia, lymphoma or sarcoidosis, that are associated with unregulated overproduction of calcitriol, supplemental vitamin D3 may worsen hypercalcemia and/or hypercalciuria. Regular monitoring of
urine and serum calcium may be indicated in this population.

Symptoms of vitamin D toxicity include hypercalcemia, hypercalciuria, anorexia, nausea, vomiting, polyuria, polydipsia, weakness and lethargy. Serum and urine calcium levels should be monitored in patients with suspected vitamin D toxicity. Standard therapy includes restriction of dietary calcium, hydration and systemic glucocorticoids in patients with severe hypercalcemia.

DOSAGE AND ADMINISTRATION

FOSTEUM should be taken twice a day, approximately 12 hours apart, and may be taken with or without food. FOSTEUM has no food limitations. There are no postural limitations. Patients taking FOSTEUM should ensure adequate calcium and vitamin D intake, as directed by a physician.

HOW SUPPLIED

FOSTEUM is an off-white capsule with "FOSTEUM" and "52003" printed in blue on the cap and body respectively. They are supplied as follows:

68040-603-16 unit-of-use bottle of 60 capsules with desiccant (30-day supply)

68040-603-08 carton of 1 5-day sample blister pack (10 capsules total)

Storage

Store at room temperature 59° – 86°F (15° – 30°C). Protect from light and moisture. Store capsules in original bottle until usage. Keep out of reach of children.

Manufactured for:
Primus Pharmaceuticals, Inc.
Scottsdale, AZ 85253
www.primusrx.com

U.S. Patent Nos. 5,935,996, 7,582,418*, 7,838,042*, and 8,338,393. Patents pending.
*Used under license from Albion Laboratories, Inc., Clearfield, UT.

©2020 Primus Pharmaceuticals, Inc. All rights reserved. 13008-1020

PRINCIPAL DISPLAY PANEL

68040-603-16

Dispensed by Prescription

Fosteum® Capsules

genistein aglycone (27 mg)
citrated zinc bisglycinate (20 mg)
cholecalciferol (200 IU)

MEDICAL FOOD PRODUCT

For the Clinical Dietary
Management of the Metabolic Processes
of Osteopenia and Osteoporosis

CONTENTS: 60 CAPSULES